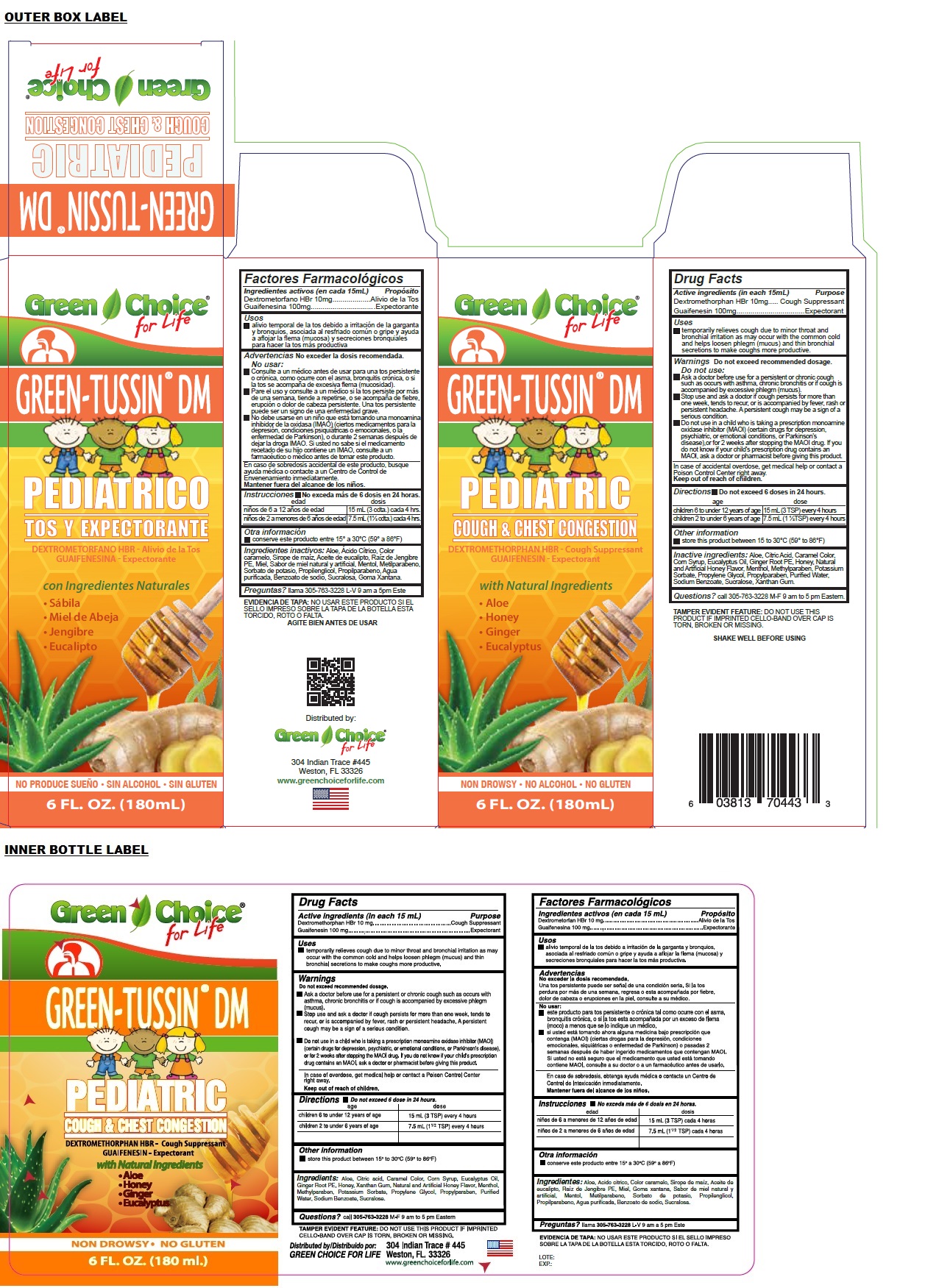 DRUG LABEL: GREEN TUSSIN DM PEDIATRIC
NDC: 55287-443 | Form: LIQUID
Manufacturer: Green Choice for Life
Category: otc | Type: HUMAN OTC DRUG LABEL
Date: 20240314

ACTIVE INGREDIENTS: DEXTROMETHORPHAN HYDROBROMIDE 10 mg/15 mL; GUAIFENESIN 100 mg/15 mL
INACTIVE INGREDIENTS: ALOE; CITRIC ACID MONOHYDRATE; CARAMEL; CORN SYRUP; EUCALYPTUS OIL; GINGER; HONEY; MENTHOL, UNSPECIFIED FORM; METHYLPARABEN; POTASSIUM SORBATE; PROPYLENE GLYCOL; PROPYLPARABEN; WATER; SODIUM BENZOATE; SUCRALOSE; XANTHAN GUM

GREEN-TUSSIN® DM PEDIATRIC

Active ingredients (in each 15 mL)

Dextromethorphan HBr 10 mg
Guaifenesin 100 mg

Purpose

Cough Suppressant
Expectorant

Uses

• temporarily relieves cough due to minor throat and bronchial irritation as may occur with the common cold and helps loosen phlegm (mucus) and thin bronchial secretions to make coughs more productive.

Warnings

Do not exceed recommended dosage.

Do not use:
• Ask a doctor before use for a persistent or chronic cough such as occurs with asthma, chronic bronchitis or if cough is accompanied by excessive phlegm (mucus).
• Stop use and ask a doctor if cough persists for more than one week, tends to recur, or is accompanied by fever, rash or persistent headache. A persistent cough may be a sign of a serious condition.
• Do not use in a child who is taking a prescription monoamine oxidase inhibitor (MAOl) (certain drugs for depression, psychiatric, or emotional conditions, or Parkinson's disease), or for 2 weeks after stopping the MAOI drug. If you do not know if your child's prescription drug contains an MAOl, ask a doctor or pharmacist before giving this product.

KEEP OUT OF REACH OF CHILDREN

In case of accidental overdose, get medical help or contact a Poison Control Center right away.
Keep out of reach of children.

Directions

• Do not exceed 6 doses in 24 hours.

age | dose
children 6 to under 12 years of age | 15 mL (3 TSP) every 4 hours
children 2 to under 6 years of age | 7.5 mL (1 ½TSP) every 4 hours

Other information

• store this product between 15 to 30°C (59° to 86°F)

Inactive ingredients:

Aloe, Citric Acid, Caramel Color, Corn Syrup, Eucalyptus Oil, Ginger Root PE, Honey, Natural and Artificial Honey Flavor, Menthol, Methylparaben, Potassium Sorbate, Propylene Glycol, Propylparaben, Purified Water, Sodium Benzoate, Sucralose, Xanthan Gum.

Questions?

call 305-763-3228 M-F 9 am to 5 pm Eastern.

COUGH & CHEST CONGESTION

with Natural Ingredients

• Aloe
• Honey
• Ginger
• Eucalyptus

NON DROWSY • NO ALCOHOL • NO GLUTEN

TAMPER EVIDENT FEATURE: DO NOT USE THIS PRODUCT IF IMPRINTED CELLO-BAND OVER CAP IS TORN, BROKEN OR MISSING.

SHAKE WELL BEFORE USING

Distributed by:
Green Choice for Life
304 Indian Trace #445
Weston, FL 33326

www.greenchoiceforlife.com